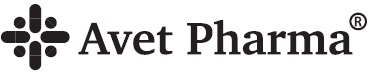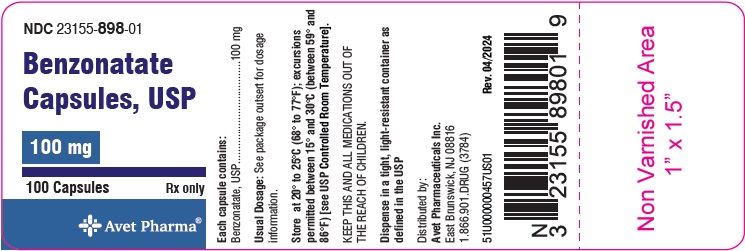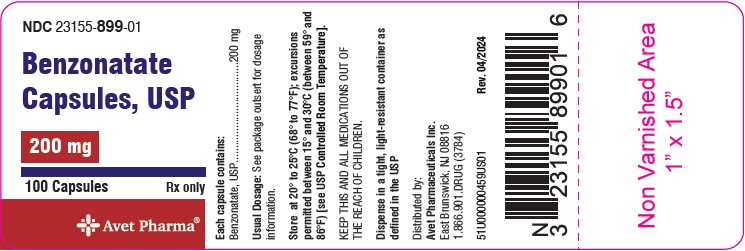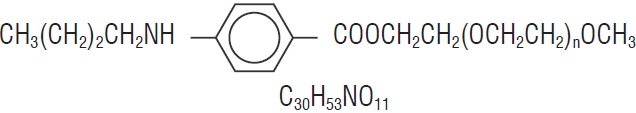 DRUG LABEL: Benzonatate
NDC: 67296-2207 | Form: CAPSULE, LIQUID FILLED
Manufacturer: Redpharm Drug
Category: prescription | Type: HUMAN PRESCRIPTION DRUG LABEL
Date: 20260128

ACTIVE INGREDIENTS: BENZONATATE 100 mg/1 1
INACTIVE INGREDIENTS: METHYLPARABEN SODIUM; PROPYLPARABEN SODIUM; GLYCERIN; GELATIN; D&C YELLOW NO. 10 ALUMINUM LAKE; AMMONIA; ISOPROPYL ALCOHOL; BUTYL ALCOHOL; PROPYLENE GLYCOL; SHELLAC; DIMETHICONE; TITANIUM DIOXIDE

Benzonatate Capsules, USP
100 mg and 200 mg
Rx Only

DESCRIPTION

Benzonatate, a non-narcotic oral antitussive agent, is 2, 5, 8, 11, 14, 17, 20, 23, 26-nonaoxaoctacosan-28-yl p-(butylamino) benzoate; with a molecular weight of 603.7.

Benzonatate Capsules, USP contain 100 mg or 200 mg of benzonatate, USP.

Benzonatate Capsules also contain: D&C Yellow No. 10, gelatin, glycerin, methylparaben sodium and propylparaben sodium.

The white imprinting ink contains the following inactive ingredients: ammonium hydroxide, isopropyl alcohol, n-butyl alcohol, propylene glycol, shellac glaze, simethicone and titanium dioxide.

FDA approved dissolution test specifications differ from USP.

CLINICAL PHARMACOLOGY

Benzonatate acts peripherally by anesthetizing the stretch receptors located in the respiratory passages, lungs, and pleura by dampening their activity and thereby reducing the cough reflex at its source. It begins to act within 15 to 20 minutes and its effect lasts for 3 to 8 hours. Benzonatate has no inhibitory effect on the respiratory center in recommended dosage.

INDICATIONS AND USAGE

Benzonatate is indicated for the symptomatic relief of cough.

CONTRAINDICATIONS

Hypersensitivity to benzonatate or related compounds.

WARNINGS

Hypersensitivity

Severe hypersensitivity reactions (including bronchospasm, laryngospasm and cardiovascular collapse) have been reported which are possibly related to local anesthesia from sucking or chewing the capsule instead of swallowing it. Severe reactions have required intervention with vasopressor agents and supportive measures.

Psychiatric Effects

Isolated instances of bizarre behavior, including mental confusion and visual hallucinations, have also been reported in patients taking benzonatate in combination with other prescribed drugs.

Accidental Ingestion and Death in Children

Keep benzonatate out of reach of children.

Accidental ingestion of benzonatate resulting in death has been reported in children below age 10.

Signs and symptoms of overdose have been reported within 15 to 20 minutes and death has been reported within one hour of ingestion. If accidental ingestion occurs, seek medical attention immediately (see OVERDOSAGE).

PRECAUTIONS

Benzonatate is chemically related to anesthetic agents of the para-amino-benzoic acid class (e.g., procaine; tetracaine) and has been associated with adverse CNS effects possibly related to a prior sensitivity to related agents or interaction with concomitant medication.

Information for Patients:

Swallow benzonatate capsules whole. Do not break, chew, dissolve, cut, or crush benzonatate capsules.

Release of benzonatate from the capsule in the mouth can produce a temporary local anesthesia of the oral mucosa and choking could occur. If numbness or tingling of the tongue, mouth, throat, or face occurs, refrain from oral ingestion of food or liquids until the numbness has resolved. If the symptoms worsen or persist, seek medical attention.

Keep benzonatate out of reach of children. Accidental ingestion resulting in death has been reported in children. Signs and symptoms of overdose have been reported within 15 to 20 minutes and death has been reported within one hour of ingestion. Signs and symptoms may include restlessness, tremors, convulsions, coma and cardiac arrest. If accidental ingestion occurs, seek medical attention immediately.

Overdosage resulting in death may occur in adults.

Do not exceed a single dose of 200 mg and a total daily dosage of 600 mg. If you miss a dose of benzonatate, skip that dose and take the next dose at the next scheduled time. Do not take 2 doses of benzonatate at one time.

Usage in Pregnancy:

Pregnancy Category C.

Animal reproduction studies have not been conducted with benzonatate. It is also not known whether benzonatate can cause fetal harm when administered to a pregnant woman or can affect reproduction capacity. Benzonatate should be given to a pregnant woman only if clearly needed.

Nursing Mothers:

It is not known whether this drug is excreted in human milk. Because many drugs are excreted in human milk, caution should be exercised when benzonatate is administered to a nursing woman.

Carcinogenesis, Mutagenesis, Impairment of Fertility:

Carcinogenicity, mutagenicity, and reproduction studies have not been conducted with benzonatate.

Pediatric Use:

Safety and effectiveness in children below the age of 10 have not been established. Accidental ingestion resulting in death has been reported in children below age 10. Keep out of reach of children.

ADVERSE REACTIONS

Potential Adverse Reactions to benzonatate may include:

Hypersensitivity reactionsincluding bronchospasm, laryngospasm, cardiovascular collapse possibly related to local anesthesia from chewing or sucking the capsule.

CNS:sedation; headache; dizziness; mental confusion; visual hallucinations.

GI:constipation; nausea; GI upset.

Dermatologic:pruritus; skin eruptions.

Other:nasal congestion; sensation of burning in the eyes; vague “chilly” sensation; numbness of the chest; hypersensitivity.

Deliberate or accidental overdose has resulted in death, particularly in children.

To report SUSPECTED ADVERSE REACTIONS, contact Avet Pharmaceuticals Inc. at 1-866-901-DRUG (3784) or FDA at 1-800-FDA-1088 or www.fda.gov/medwatch.

OVERDOSAGE

Intentional and unintentional overdose may result in death, particularly in children.

The drug is chemically related to tetracaine and other topical anesthetics and shares various aspects of their pharmacology and toxicology. Drugs of this type are generally well absorbed after ingestion.

Signs and Symptoms:

The signs and symptoms of overdose of benzonatate have been reported within 15 to 20 minutes. If capsules are chewed or dissolved in the mouth, oropharyngeal anesthesia will develop rapidly, which may cause choking and airway compromise.

CNS stimulation may cause restlessness and tremors, which may proceed to clonic convulsions followed by profound CNS depression. Convulsions, coma, cerebral edema and cardiac arrest leading to death have been reported within 1 hour of ingestion.

Treatment:

In case of overdose, seek medical attention immediately. Evacuate gastric contents and administer copious amounts of activated charcoal slurry. Even in the conscious patient, cough and gag reflexes may be so depressed as to necessitate special attention to protection against aspiration of gastric contents and orally administered materials. Convulsions should be treated with a short-acting barbiturate given intravenously and carefully titrated for the smallest effective dosage. Intensive support of respiration and cardiovascular-renal function is an essential feature of the treatment of severe intoxication from overdosage.

Do not use CNS stimulants.

DOSAGE AND ADMINISTRATION

Adults and Children over 10 years of age:

Usual dose is one 100 mg or 200 mg capsule three times a day as needed for cough. If necessary to control cough, up to 600 mg daily in three divided doses may be given . Benzonatate should be swallowed whole.Benzonatate Capsules are not to be broken, chewed, dissolved, cut or crushed.

HOW SUPPLIED

Benzonatate Capsules, USP are available as:

100 mgOval Shape, imprint “100” with white ink, transparent yellow soft gelatin capsule

NDC 23155-898-01 Bottles of 100

NDC 23155-898-05 Bottles of 500

200 mgOblong Shape, imprint “200” with white ink, transparent yellow soft gelatin capsules

NDC 23155-899-01 Bottles of 100

NDC 23155-899-05 Bottles of 500

Store at 20° to 25°C (68° to 77°F); excursions permitted to 15° to 30°C (59° to 86°F) [See USP Controlled Room Temperature].Dispense in tight, light-resistant container as defined in the USP.

Distributed by:

Avet Pharmaceuticals Inc.

East Brunswick, NJ 08816

1.866.901.DRUG (3784)

51U000000461US01

Revised: 04/2024

PACKAGE LABEL.PRINCIPAL DISPLAY PANEL - 100 mg

NDC23155- 898-01

Benzonatate Capsules, USP

100 mg

100 Capsules

Rx only

PACKAGE LABEL.PRINCIPAL DISPLAY PANEL - 200 mg

NDC23155- 899-01

Benzonatate Capsules, USP

200 mg

100 Capsules

Rx only